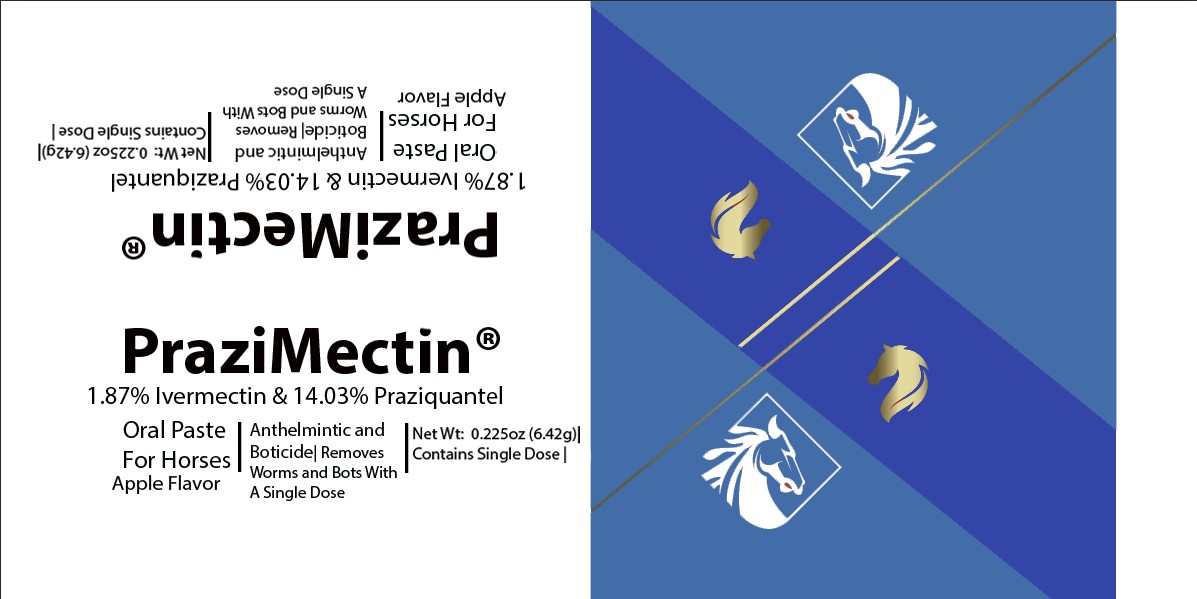 DRUG LABEL: Prazimectin
NDC: 86213-773 | Form: PASTE
Manufacturer: Vetr, LLC
Category: animal | Type: OTC ANIMAL DRUG LABEL
Date: 20250825

ACTIVE INGREDIENTS: IVERMECTIN 18.7 mg/1 g; PRAZIQUANTEL 140 mg/1 g
INACTIVE INGREDIENTS: GLYCERIN; POTASSIUM SORBATE; METHYLPARABEN; PROPYLPARABEN

Vetr Prazimectin (14.03% Praziquantel, 1.87% ivermectin oral paste)

Animal Safety

Not safe or approved for human use. May be used in horses of all ages including mares at any stage of pregnancy. KEEP OUT OF REACH OF CHILDREN.

Directions for Use

One syringe contains sufficient paste to treat one 1250 lb horse at the recommended dose rate (0.2 mg/kg) body weight. Do not underdose. Ensure each animal receives a complete dose based on a current body weight. Underdosing may result in ineffective treatment, and encourage the development of parasite resistance.

Storage

Store at room temperature, 20-25 C (68-77 F)

Active Ingredients

Praziquantel USP, 140 mg/g (14.03% w/w); Ivermectin USP, 18.7 mg/g (1.87% w/w)

Other Ingredients

Certified vegetable glycerine, natural preservative, stabilizers and flavoring